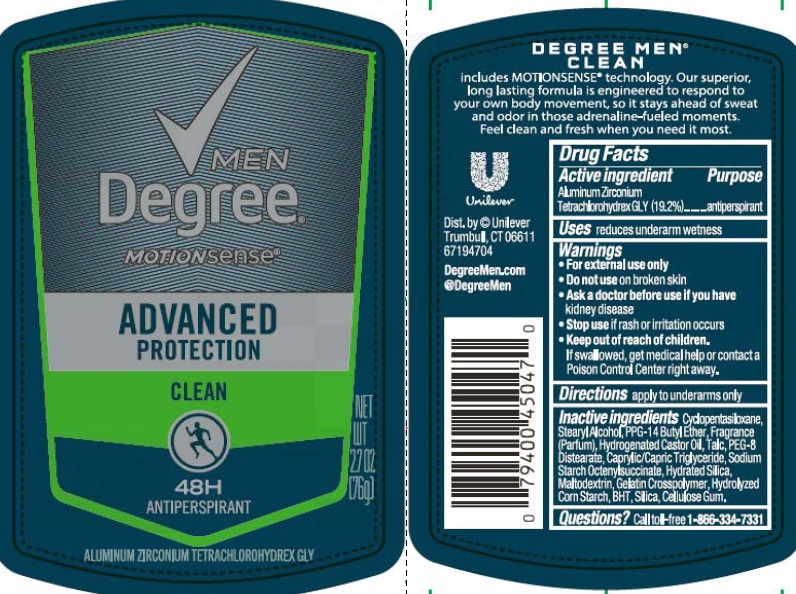 DRUG LABEL: Degree Men
NDC: 64942-1501 | Form: STICK
Manufacturer: Conopco Inc. d/b/a/ Unilever
Category: otc | Type: HUMAN OTC DRUG LABEL
Date: 20211201

ACTIVE INGREDIENTS: ALUMINUM ZIRCONIUM TETRACHLOROHYDREX GLY 19.2 g/100 g
INACTIVE INGREDIENTS: CARBOXYMETHYLCELLULOSE SODIUM; PEG-8 DISTEARATE; HYDRATED SILICA; BUTYLATED HYDROXYTOLUENE; MALTODEXTRIN; STARCH, CORN; SILICON DIOXIDE; CYCLOMETHICONE 5; STEARYL ALCOHOL; PPG-14 BUTYL ETHER; HYDROGENATED CASTOR OIL; TALC; MEDIUM-CHAIN TRIGLYCERIDES

Degree Men Morionsense Advanced Protection Clean 48H Antiperspirant - aluminum zirconium tetrachlorohydrex gly stick

Degree Men Morionsense Advanced Protection Clean 48H Antiperspirant

Drug Facts Active ingredient

Aluminum Zirconium Tetrachlorohydrex GLY (19.2 %)

Purpose

antiperspirant

Uses

reduces underarm wetness

Warnings

• For external use only.

• Do not use on broken skin.

• Ask a doctor before use if you have kidney disease.

• Stop use if rash or irritation occurs.

• Keep out of reach of children.
If swallowed, get medical help or contact a Poison Control Center right away.

Directions

apply to underarms only

Inactive ingredients

Cyclopentasiloxane, Stearyl Alcohol, PPG-14 Butyl Ether, Fragrance (Parfum), Hydrogenated Castor Oil, Talc, PEG-8 Distearate, Caprylic/Capric Triglyceride, Sodium Starch Octenylsuccinate, Hydrated Silica, Maltodextrin, Gelatin Crosspolymer, Hydrolyzed Corn Starch, BHT, Silica, Cellulose Gum

Questions?

Call toll-free 1-866-334-7331